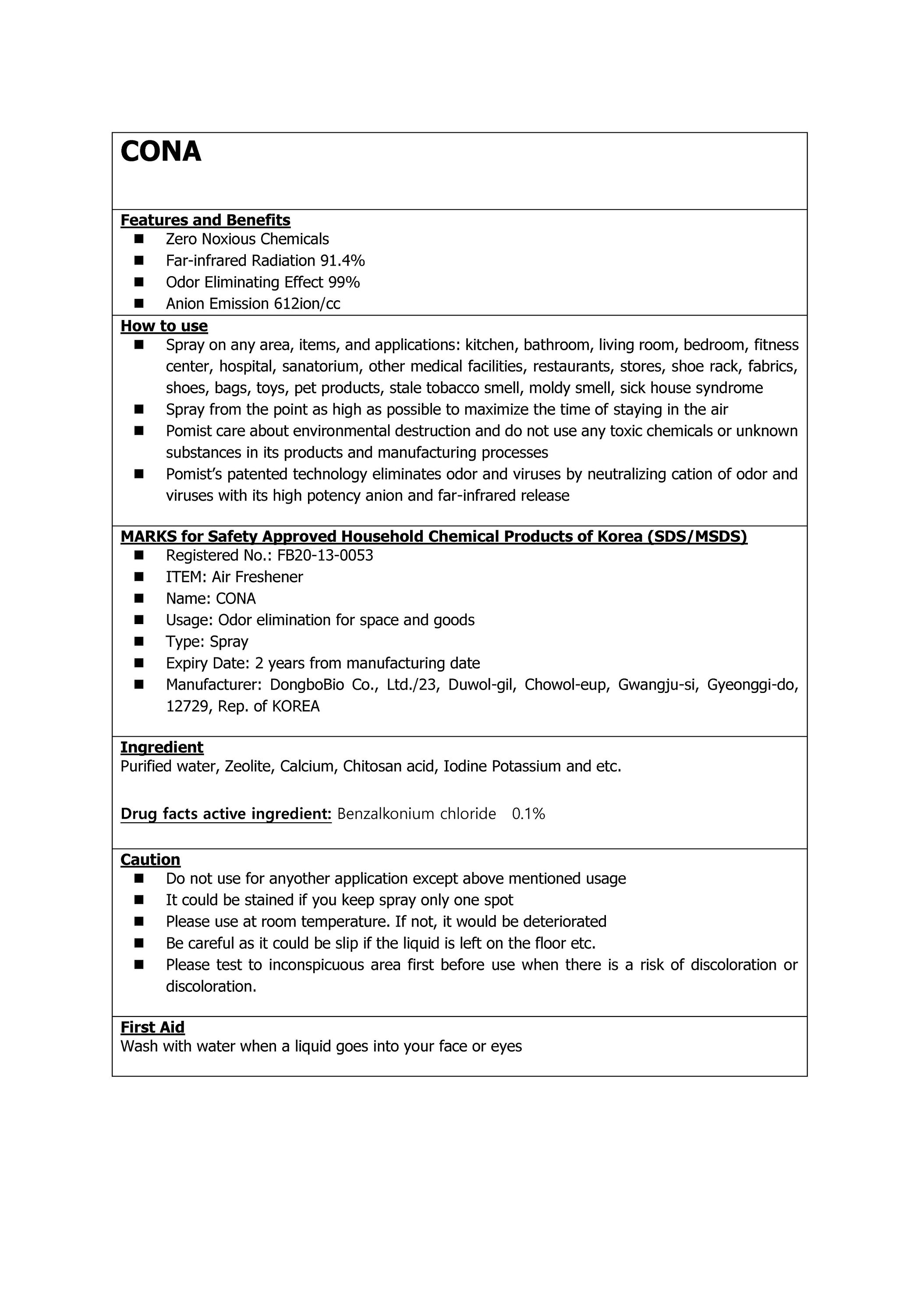 DRUG LABEL: CONA
NDC: 74651-0003 | Form: LIQUID
Manufacturer: DONGBO BIO CO.,LTD
Category: otc | Type: HUMAN OTC DRUG LABEL
Date: 20200911

ACTIVE INGREDIENTS: BENZALKONIUM CHLORIDE 1 g/100 mL
INACTIVE INGREDIENTS: BENTONITE; WATER; CALCIUM; CHITOSAN OLIGOSACCHARIDE; IODINE; ZEOLITE A; SODIUM MOLYBDATE

ACTIVE INGREDIENT

Benzalkonium chloride

INACTIVE INGREDIENT

Water, zeolite, calcium, bentonite, chitosan, sericite, sulfate, iodine, sodium molybdate

PURPOSE

Zero Noxious Chemicals

Far-infrared Radiation 91.4%

Odor Eliminating Effect 99%

Anion Emission 612ion/cc

WARNINGS

■ if following abnormal symptoms persist, discontinue use

Irritation around the eyes, ears, mucous membranes, including the mouth, under the skin irritation and rashes

■ Stop immediately and consult a doctor if you experience

1) Hypersensitivity symptoms such as erythema, itching and dermatitis.

2) Skin Irritation

3) Following Instructions when using medication

(1) For external use only (Do not use internally)

(2) Avoid getting into the eyes (if contact occurs, wash well with clean water)

■ Be careful not to inhale or use excessively for a long time (ingesting ethanol repeatedly causes irritation to mucous membranes and headaches or other symptoms may appear. When used repeatedly in the same area, skin irritation may occur.

■ Do not use the product for a long time in the same area as swelling, inflammation or sickness may occur due to absorption through the skin.

It is not recommended to use this one areas that have been medically treated with a cast or bandage.

■ Do not use in combination with soap or antibacterial cleansing agents.

• Keep Out of Reach of Children.

INDICATIONS AND USAGE

Spray on any area, items, and applications: kitchen, bathroom, living room, bedroom, fitness center, hospital, sanatorium, other medical facilities, restaurants, stores, shoe rack, fabrics, shoes, bags, toys, pet products, stale tobacco smell, moldy smell, sick house syndrome

Spray from the point as high as possible to maximize the time of staying in the air

Pomist care about environmental destruction and do not use any toxic chemicals or unknown substances in its products and manufacturing processes

Pomist’s patented technology eliminates odor and viruses by neutralizing cation of odor and viruses with its high potency anion and far-infrared release

DOSAGE AND ADMINISTRATION

for topical use only